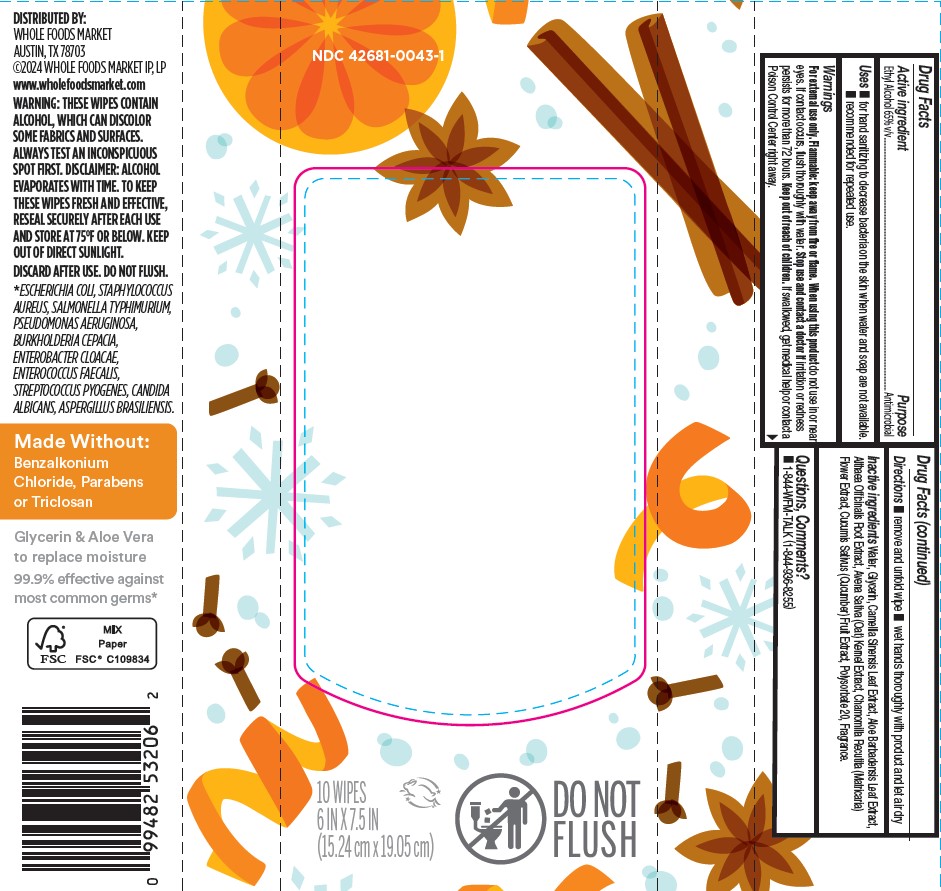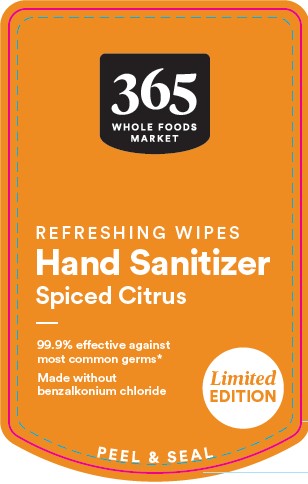 DRUG LABEL: 365 Spiced Citrus Hand Sanitizer Wipes
NDC: 42681-0043 | Form: CLOTH
Manufacturer: Whole Foods Market, Inc.
Category: otc | Type: HUMAN OTC DRUG LABEL
Date: 20251008

ACTIVE INGREDIENTS: ALCOHOL 2.55 mL/1 1
INACTIVE INGREDIENTS: POLYSORBATE 20; OAT; WATER; ALOE VERA LEAF; ALTHAEA OFFICINALIS ROOT; GLYCERIN; GREEN TEA LEAF; CHAMOMILE; CUCUMBER

365 Spiced Citrus Hand Sanitizer Wipes

Active Ingredient

Ethyl Alcohol 65% v/v

Purpose

Antimicrobial

Uses

■ for hand sanitizing to decrease bacteria on the skin when water and soap are not available.
■ recommended for repeated use.

Warnings

For external use only. Flammable: keep away from fire or flame. When using this product do not use in or near eyes. If contact occurs, flush thoroughly with water. Stop use and contact a doctor if irritation or redness persists for more than 72 hours.

Keep out of reach of children unless under adult supervision. If swallowed, get medical help or contact a Poison Control Center right away.

Directions

■ remove and unfold wipe ■ wet hands thoroughly with product and let air dry

Inactive ingredients

Water, Glycerin, Camellia Sinensis Leaf Extract, Aloe Barbadensis Leaf Extract, Althaea Officinalis Root Extract, Avena Sativa (Oat) Kernel Extract, Chamomilla Recutita (Matricaria) Flower Extract, Cucumis Sativus (Cucumber) Fruit Extract, Polysorbate 20, Fragrance.

Questions, Comments?

■ 1-844-WFM-TALK (1-844-936-8255)

Principal Display Panel

NDC 42681-0043-1

365 WHOLE FOODS MARKET

REFRESHING WIPES

Hand Sanitizer

Spiced Citrus

99.9% effective against most common germs*

Made without benzalkonium chloride

Limited EDITION

PEEL & SEAL

10 WIPES

6 IN X 7.5 IN
(15.24 cm x 19.05 cm)

DO NOT FLUSH

Drug Facts

Active Ingredient Purpose

Ethyl Alcohol 65% v/v.................Antimicrobial

Uses ■ for hand sanitizing to decrease bacteria on the skin when water and soap are not available.
■ recommended for repeated use.

Warnings
For external use only. Flammable: keep away from fire or flame. When using this product do not use in or near eyes. If contact occurs, flush thoroughly with water. Stop use and contact a doctor if irritation or redness persists for more than 72 hours. Keep out of reach of children unless under adult supervision. If swallowed, get medical help or contact a Poison Control Center right away.

Directions ■ remove and unfold wipe ■ wet hands thoroughly with product and let air dry

Inactive ingredients Water, Glycerin, Camellia Sinensis Leaf Extract, Aloe Barbadensis Leaf Extract, Althaea Officinalis Root Extract, Avena Sativa (Oat) Kernel Extract, Chamomilla Recutita (Matricaria) Flower Extract, Cucumis Sativus (Cucumber) Fruit Extract, Polysorbate 20, Fragrance.

Questions, Comments? ■ 1-844-WFM-TALK (1-844-936-8255)

DISTRIBUTED BY:
WHOLE FOODS MARKET
AUSTIN, TX 78703
©2024 WHOLE FOODS MARKET IP, LP
www.wholefoodsmarket.com
WARNING: THESE WIPES CONTAIN ALCOHOL, WHICH CAN DISCOLOR SOME FABRICS AND SURFACES. ALWAYS TEST AN INCONSPICUOUS SPOT FIRST. DISCLAIMER: ALCOHOL EVAPORATES WITH TIME. TO KEEP THESE WIPES FRESH AND EFFECTIVE, RESEAL SECURELY AFTER EACH USE AND STORE AT 75°F OR BELOW. KEEP OUT OF DIRECT SUNLIGHT. DISCARD AFTER USE. DO NOT FLUSH.

*ESCHERICHIA COLI, STAPHYLOCOCCUS AUREUS, SALMONELLA TYPHIMURIUM, PSEUDOMONAS AERUGINOSA, BURKHOLDERIA CEPACIA, ENTEROBACTER CLOACAE, ENTEROCOCCUS FAECALIS, STREPTOCOCCUS PYOGENES, CANDIDA ALBICANS, ASPERGILLUS BRASILIENSIS.

Made Without:

Benzalkonium Chloride, Parabens or Triclosan

Glycerin & Aloe Vera to replace moisture

99.9% effective against most common germs*

FSC MIX Paper

FSC® C109834

0 99482 53206 2